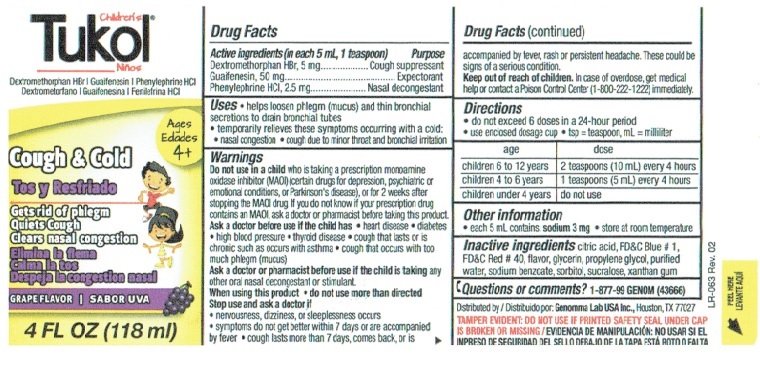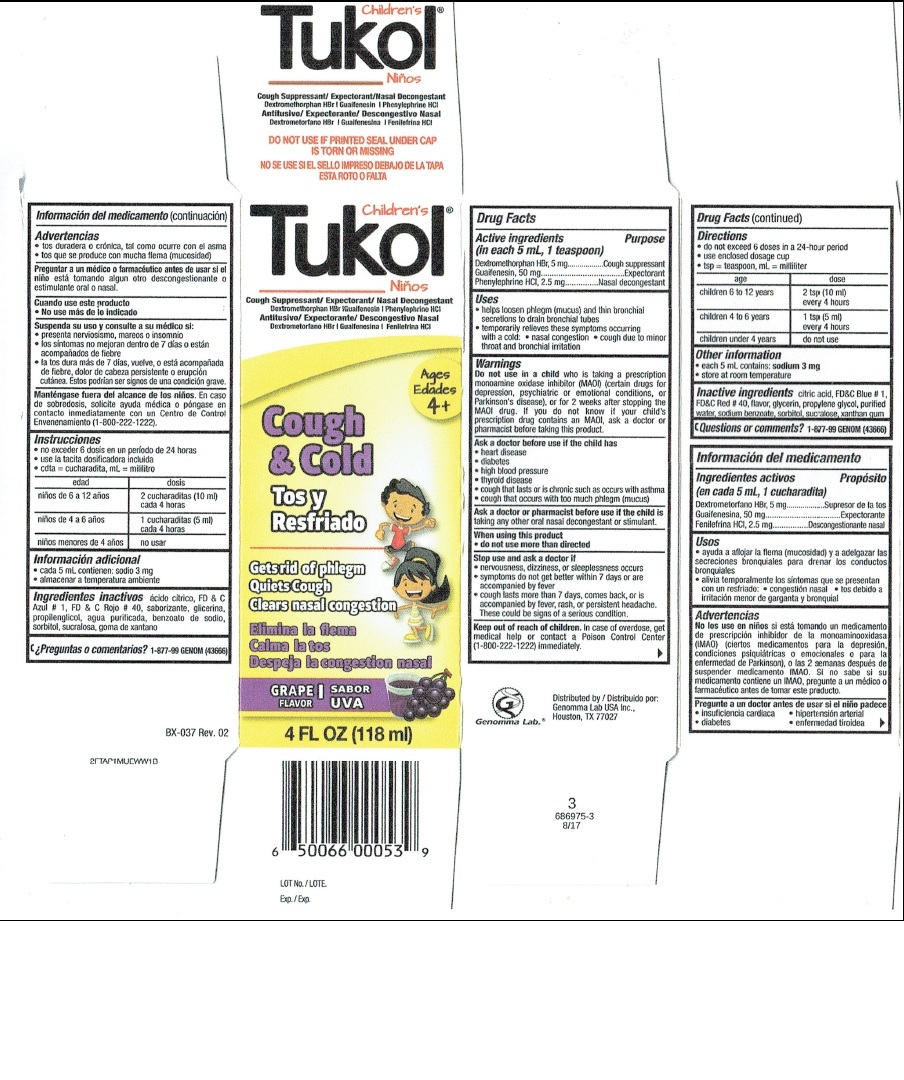 DRUG LABEL: Tukol A
NDC: 50066-536 | Form: LIQUID
Manufacturer: Genomma Lab USA, Inc.
Category: otc | Type: HUMAN OTC DRUG LABEL
Date: 20171228

ACTIVE INGREDIENTS: DEXTROMETHORPHAN HYDROBROMIDE 5 mg/5 mL; GUAIFENESIN 50 mg/5 mL; PHENYLEPHRINE HYDROCHLORIDE 2.5 mg/5 mL
INACTIVE INGREDIENTS: ANHYDROUS CITRIC ACID; FD&C BLUE NO. 1; FD&C RED NO. 40; GLYCERIN; WATER; SODIUM BENZOATE; SORBITOL; SUCRALOSE; XANTHAN GUM

Active ingredients

DRUG FACTS
Active ingredients
(in each 5 mL, 1 teaspoon)
Dextromethorphan HBr, USP 5 mg
Guaifenesin, USP 50 mg
Phenylephrine HCL, USP 2.5 mg

Purpose

Cough Suppressant
Expectorant
Nasal Decongestant

Uses

- help loosen phlegm (mucus) and thin bronchial secretions to drain bronchial tubes

- temporarily relieves these symptoms occurring with a cold - nasal congestion - cough due to minor throat and bronchial irritation

Warnings

Do not use in a child

who is taking a prescription monoamine oxidase inhibitor (MAOI) (certain drugs for depression, psychiatric, or emotional conditions, or Parkinson's disease), or for 2 weeks after stopping the MAOI drug. If you do not know if your child's prescription drug contains an MAOI, ask a doctor or pharmacist before taking this product.

Ask a doctor before use if the child has

- heart disease
- diabetes
- high blood pressure
- thyroid disease
- cough that lasts or is chronic such as occurs with asthma
- cough that occurs with too much phlegm (mucus)

Ask a doctor or pharmacist before use if the child is

taking any other oral nasal decongestant or stimulant.

When using this product

- do not use more than directed

Stop use and ask a doctor if

- nervousness, dizziness, or sleeplessness occurs
- symptoms do not get better within 7 days or are accompanied by a fever
- cough lasts more than 7 days, comes back, or is accompanied by fever, rash, or persistent headache These could be signs of a serious condition.

Keep out of reach of children

In case of overdose, get medical help or contact a Poison Control Center (1-800-222-1222) immediately.

Directions

age dose

children 6 to 12 years 2 tsp (10 mL) every 4 hours

children 4 to 6 years 1 tsp (5 mL) every 4 hours

children under 4 years do not use

- do not exceed 6 doses in a 24-hour period
- use enclosed dosage cup
- tsp = teaspoon, mL = milliliter

Other information

- each 5 mL contains: sodium 3 mg
- store at room temperature

Inactive ingredients

citric acid, FD and C Blue # 1, FD and C Red # 40, flavor, glycerin, purified water, sodium benzoate, sorbitol, sucralose, xanthan gum

Questions or comments?

1 877 99 GENOM (43666)

Children's Tukol Bottle Label

Children’s Tukol®

Cough Suppressant/Expectorant/Nasal Decongestant
Dextromethorphan HBr | Guaifenesin | Phenylephrine HCI

Ages 4+

Cough and Cold

Gets rid of phlegm
Quiets Cough
Clears nasal congestion

Grape Flavor

4 FL OZ (118 ml)

Drug Facts

Active ingredients Purpose
(in each 5 mL, 1 teaspoon)
Dextromethorphan HBr, 5 mg ...............Cough suppressant
Guaifenesin, 50 mg. .......................................Expectorant
Phenylephrine HCI, 2.5 mg ................... Nasal decongestant

Uses
• helps loosen phlegm (mucus) and thin bronchial secretions to drain bronchial tubes
• temporarily relieves these symptoms occurring with a cold:
• nasal congestion
• cough due to minor throat and bronchial irritation

Warnings

Do not use in a child who is taking a prescription monoamine oxidase inhibitor (MAOI) (certain drugs for depression, psychiatric or emotional conditions, or Parkinson's disease), or for 2 weeks after stopping the MAOI drug. If you do not know if your prescription drug contains an MAOI, ask a doctor or pharmacist before taking this product.

Ask a doctor before use if the child has
• heart disease
• diabetes
• high blood pressure
• thyroid disease
• cough that lasts or is chronic such as occurs with asthma
• cough that occurs with too much phlegm (mucus)

Ask a doctor or pharmacist before use if the child is taking any other oral nasal decongestant or stimulant.

When using this product
• do not use more than directed

Stop use and ask a doctor if
• nervousness, dizziness, or sleeplessness occurs
• symptoms do not get better within 7 days or are accompanied by fever
• cough last more than 7 days, comes back, or is accompanied by fever, rash or persistent headache. These could be signs of a serious condition.

Drug Facts (continued)

Keep out of reach of children. In case of overdose, get medical help or contact a Poison Control Center (1-800-222-1222) immediately.

Directions
• do not exceed 6 doses in a 24-hour period
• use enclosed dosage cup
• tsp = teaspoon, mL = milliliter

age dose
children 6 to 12 years 2 teaspoons (10 mL) every 4 hours
children 4 to 6 years 1 teaspoons (5 mL) every 4 hours
children under 4 years do not use

Other information
• each 5 mL contains: sodium 3 mg
• store at room temperature

Inactive ingredients citric acid, FD&C Blue # 1, FD&C Red # 40, flavor, glycerin, propylene glycol, purified water, sodium benzoate, sorbitol, sucralose, xanthan gum

Questions or comments? 1-877-99 GENOM (43666)

Distributed by Genomma Lab USA., Houston, TX, 77027

TAMPER EVIDENT: DO NOT USE IF PRINTED SAFETY SEAL UNDER CAP IS BROKEN OR MISSING.

LR-063 Rev. 2

PEEL HERE

Children's Tukol Box Label

Children’s Tukol®

Cough Suppressant/Expectorant/Nasal Decongestant
Dextromethorphan HBr | Guaifenesin | Phenylephrine HCI

DO NOT USE IF PRINTED SEAL UNDER CAP
IS TORN OR MISSING

Children’s Tukol®
Cough Suppressant/Expectorant/Nasal Decongestant
Dextromethorphan HBr | Guaifenesin | Phenylephrine HCI

Ages 4+

Cough and Cold

Gets rid of phlegm
Quiets Cough
Clears nasal congestion

Grape Flavor

4 FL OZ (118 ml)

LOT No.
Exp.

Drug Facts

Active ingredients Purpose
(in each 5 mL, 1 teaspoon)
Dextromethorphan HBr, 5 mg ...............Cough suppressant
Guaifenesin, 50 mg. .......................................Expectorant
Phenylephrine HCI, 2.5 mg ................... Nasal decongestant

Uses
• helps loosen phlegm (mucus) and thin bronchial secretions to drain bronchial tubes
• temporarily relieves these symptoms occurring with a cold:
• nasal congestion
• cough due to minor throat and bronchial irritation

Warnings

Do not use in a child who is taking a prescription monoamine oxidase inhibitor (MAOI) (certain drugs for depression, psychiatric or emotional conditions, or Parkinson's disease), or for 2 weeks after stopping the MAOI drug. If you do not know if your prescription drug contains an MAOI, ask a doctor or pharmacist before taking this product.

Ask a doctor before use if the child has
• heart disease
• diabetes
• high blood pressure
• thyroid disease
• cough that lasts or is chronic such as occurs with asthma
• cough that occurs with too much phlegm (mucus)

Ask a doctor or pharmacist before use if the child is taking any other oral nasal decongestant or stimulant.

When using this product
• do not use more than directed

Stop use and ask a doctor if
• nervousness, dizziness, or sleeplessness occurs
• symptoms do not get better within 7 days or are accompanied by fever
• cough last more than 7 days, comes back, or is accompanied by fever, rash or persistent headache. These could be signs of a serious condition.

Keep out of reach of children. In case of overdose, get medical help or contact a Poison Control Center (1-800-222-1222) immediately.

Distributed by
Genomma Lab USA Inc.,
Houston, TX 77027
Genomma Lab.®

3
66975-3
8/17

Drug Facts (continued)

Directions
• do not exceed 6 doses in a 24-hour period
• use enclosed dosage cup
• tsp = teaspoon, mL = milliliter

age dose
children 6 to 12 years 2 teaspoons (10 mL) every 4 hours
children 4 to 6 years 1 teaspoons (5 mL) every 4 hours
children under 4 years do not use

Other information
• each 5 mL contains: sodium 3 mg
• store at room temperature

Inactive ingredients citric acid, FD&C Blue # 1, FD&C Red # 40, flavor, glycerin, propylene glycol, purified water, sodium benzoate, sorbitol, sucralose, xanthan gum

Questions or comments? 1-877-99 GENOM (43666)

BX-037 Rev. 02
2FTAP1MUEWW1B